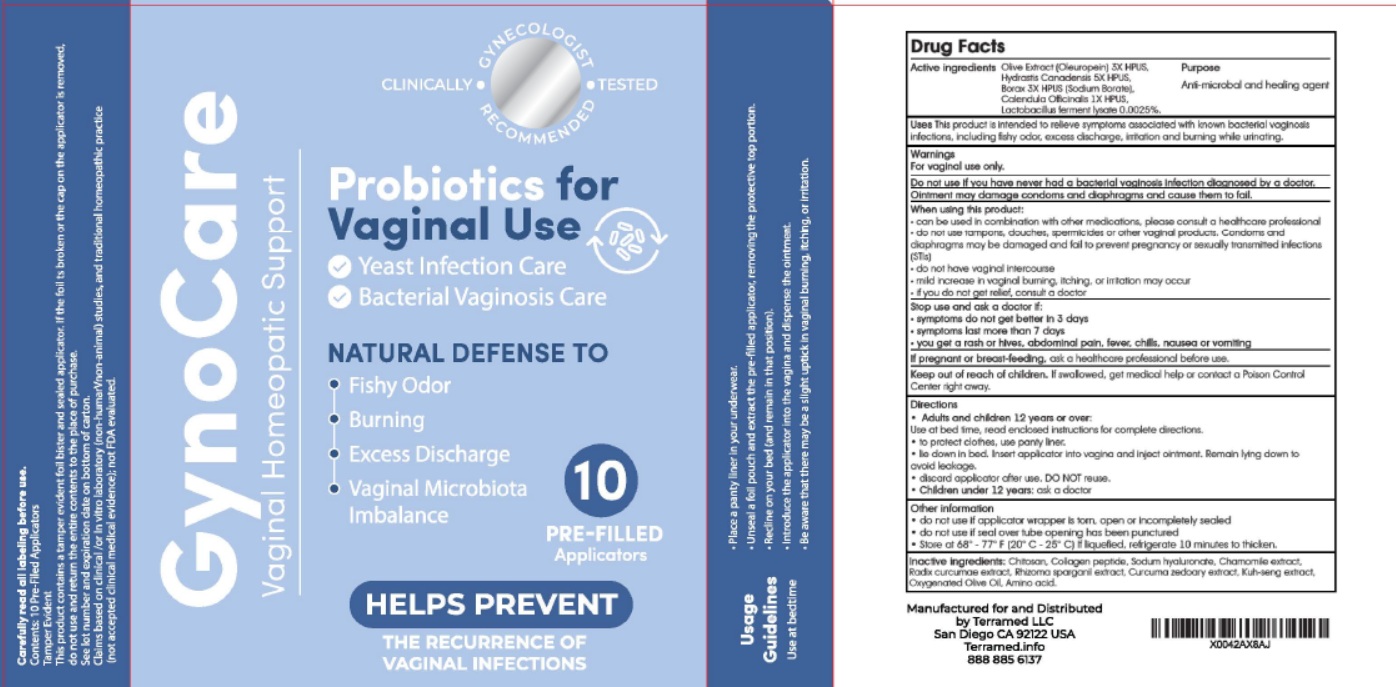 DRUG LABEL: Terramed Just Think Comfort GynoCare Probiotics for Vaginal Use
NDC: 83004-023 | Form: OINTMENT
Manufacturer: Rida LLC
Category: homeopathic | Type: HUMAN OTC DRUG LABEL
Date: 20250321

ACTIVE INGREDIENTS: OLEUROPEIN 3 [hp_X]/1 1; GOLDENSEAL 5 [hp_X]/1 1; SODIUM BORATE 3 [hp_X]/1 1; CALENDULA OFFICINALIS WHOLE 1 [hp_X]/1 1; LIMOSILACTOBACILLUS FERMENTUM 0.0025 g/1 1
INACTIVE INGREDIENTS: POLIGLUSAM; HYALURONATE SODIUM; CHAMOMILE; OLIVE OIL; AMINO ACIDS, SOURCE UNSPECIFIED; COLLAGEN, SOLUBLE, FISH SKIN; TURMERIC; CURCUMA ZEDOARIA ROOT; PUERARIA MONTANA VAR. LOBATA ROOT

Active Ingredient

Olive Extract (Oleuropein) 3X HPUS
Hydrastis Canadensis 5X HPUS,
Borax 3X HPUS (Sodium Borate)
Calendula Officinalis 1X HPUS,
Lactobacillus fermentum 0.0025%.

Purpose

Anti-microbal and healing agent

Uses

This product is intended to relieve symptoms associated with known bacterial vaginosis infections, including fishy odor, excess discharge, irritation and burning while urinating.

Warnings

For vaginal use only.

- Do not use if you have never had a bacterial vaginosis infection diagnosed by a doctor.
- Oinment may damage condoms and diaphragms and cause them to fail

When using this product

- can be used in combination with other medications, please consult a healthcare professional
- do not use tampons, douches, spermicides or other vaginal products. Condoms and diaphragms may be damaged and fail to prevent pregnancy or sexually transmitted infections
- do not have vaginal intercourse
- mild increase in vaginal burning, itching, or irritation may occur
- if you do not get relief, consult a doctor

Stop use and ask a doctor if :

- symptoms do not get better in 3 days
- symptoms last more than 7 days
- you get a rash or hives, addominal pain, fever, chills, nausea or vomtting
- if pregnant or breast-feeding ask a healthcare professional before use
- keep out of reach of children. If swallowed , get medical help or Contact a Poison Control Center right away

Directions

Adults and children 12 years or over:

Use at bed time, read enclosed instructions for complete directions.

to protect cloths, use panty liner

lie down in bed. Insert applicator into vagina and inject ointment. Remain lying down to avoid leakage

discard applicator after use. DO NOT reuse.

children under 12 years : ask a doctor

Other Information

- do not use if applicator wrappear is torn, open or incompletely sealed
- do not use if seal over tube opening has been punctured
- store at 68° - 77° F (20° to 25° C) if liquefied, refrigerate 10minutes to thicken.

Inactive ingredients

Chitosan, Collagen peptide, Sodium hyaluronate, Chamomile extract, Radix curcumae extract. Rhizome spaganil extract, Curcuma zedoary extract, Kuh-seng extract, Oxygenated Olive Oil, Amino acid.